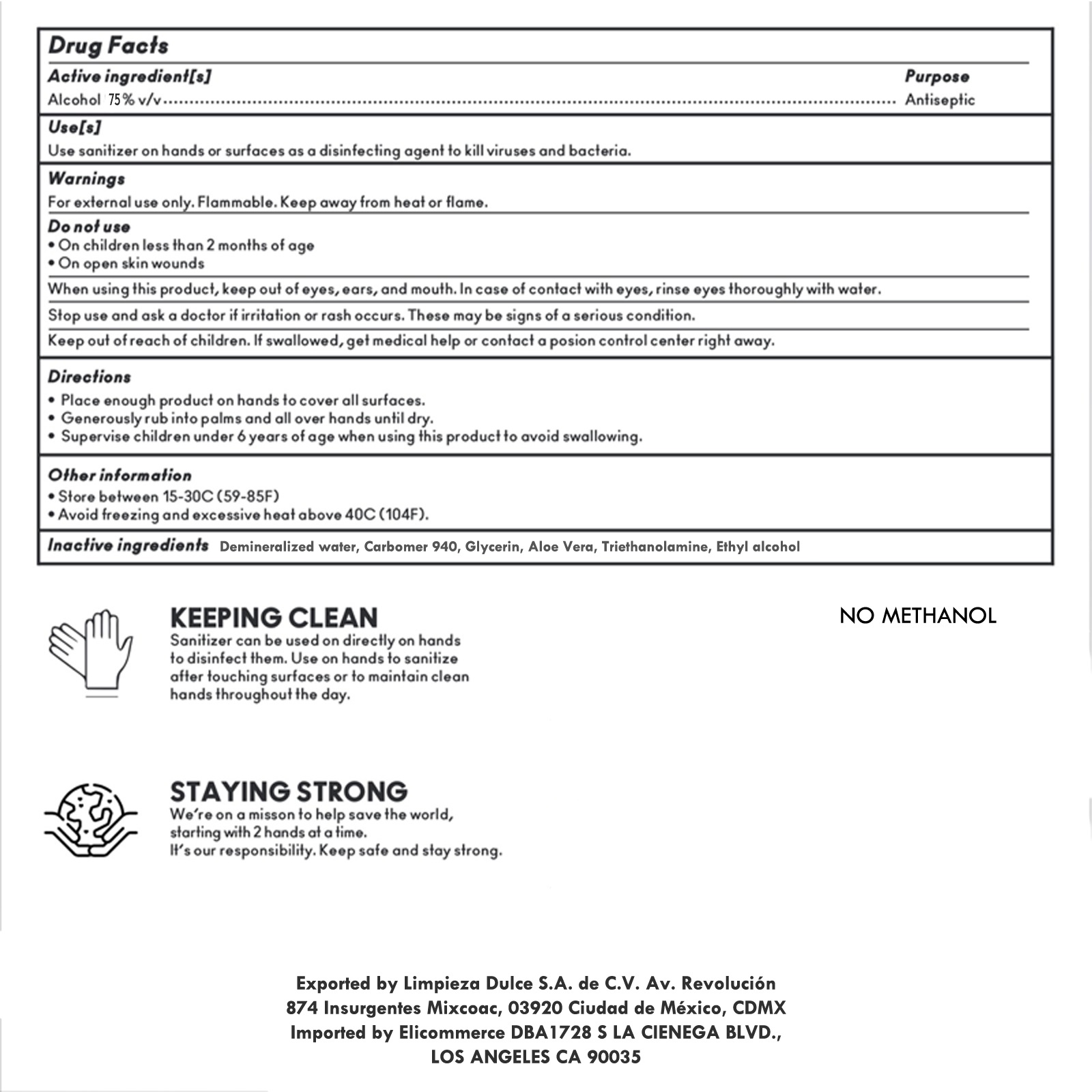 DRUG LABEL: Gel Hand Sanitizer
NDC: 79902-000 | Form: GEL
Manufacturer: Limpieza Dulce, S.A. de C.V.
Category: otc | Type: HUMAN OTC DRUG LABEL
Date: 20200901

ACTIVE INGREDIENTS: ALCOHOL 0.75 mL/1 mL
INACTIVE INGREDIENTS: WATER; CARBOMER HOMOPOLYMER TYPE C (ALLYL PENTAERYTHRITOL CROSSLINKED); GLYCERIN; ALOE VERA LEAF; TROLAMINE

Gel Hand Sanitizer

Active Ingredient[s]

Alcohol 75% v/v

Purpose

Antiseptic

Use[s]

Use sanitizer on hands or surfaces as a disinfecting agent to kill viruses and bacteria.

Warnings

For external use only. Flammable. Keep away from heat or flame.

Do not use

- On children less than 2 months of age
- On open skin wounds

When using this product,

keep out of eyes, ears, and mouth. In case of contact with eyes, rinse eyes thoroughly with water.

Stop use and ask a doctor

if irritation or rash occurs. These may be signs of a serious condition.

Keep out of reach of children.

If swallowed, get medical help or contact a poison control center right away.

Directions

- Place enough product on hands to cover all surfaces.
- Generously rub into palms and all over hands until dry.
- Supervise children under 6 years of age when using this product to avoid swallowing.

Other information

- Store between 15-30C (59-86F)
- Avoid freezing and excessive heat above 40C (104F)

Inactive ingredients

Demineralized water, Carbomer 940, Glyerin, Aloe Vera, Triethanolamine, Ethyl alcohol